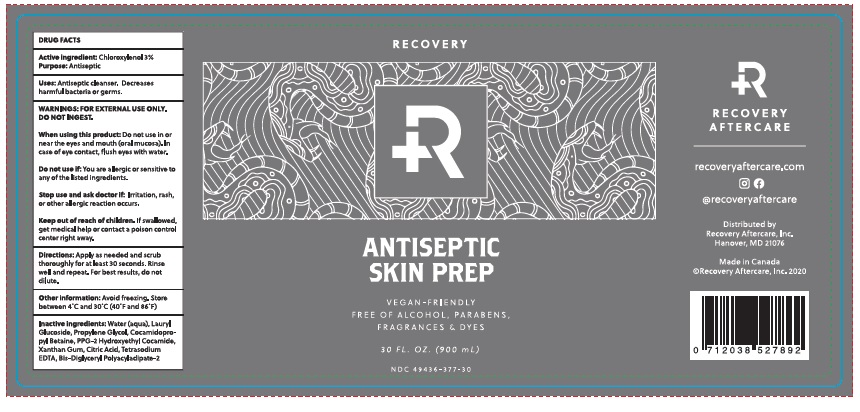 DRUG LABEL: Recovery Antiseptic Skin Prep
NDC: 49436-377 | Form: LOTION
Manufacturer: PURKLENZ FORMULATIONS INC.
Category: otc | Type: HUMAN OTC DRUG LABEL
Date: 20251112

ACTIVE INGREDIENTS: CHLOROXYLENOL 3.0 g/100 mL
INACTIVE INGREDIENTS: WATER; LAURYL GLUCOSIDE; PROPYLENE GLYCOL; COCAMIDOPROPYL BETAINE; PPG-2 HYDROXYETHYL COCAMIDE; XANTHAN GUM; CITRIC ACID MONOHYDRATE; EDETATE SODIUM; BIS-DIGLYCERYL POLYACYLADIPATE-2

Recovery Antiseptic Skin Prep

DRUG FACTS

Active ingredient: Chloroxylenol 3%

Purpose: Antiseptic

INDICATIONS AND USAGE

Uses: Antiseptic cleanser.

Decreases harmful bacteria or germs.

WARNINGS: FOR EXTERNAL USE ONLY.

DO NOT INGEST.

When using this product: Do not use in

or near the eyes and mouth (oral mucosa). In

case of eye contact, flush eyes with water.

Do not use if: you are allergic or sensitive to any of the listed ingredients.

Stop use and ask doctor if: Irritation, rash, or other allergic reaction occurs.

Keep out of reach of children. If swallowed, get medical help or contact a poison control center right away.

DOSAGE AND ADMINISTRATION

Directions: Apply as needed and scrub thoroughly for at least 30 seconds. Rinse well and repeat. For best results, do not dilute.

Other information: Avoid freezing. Store between 4˚C and 30˚C (40˚F and 86˚F)

Other information: Avoid freezing. Store between 4˚C and 30˚C (40˚F and 86˚F)

INACTIVE INGREDIENT

Inactive ingredients: Water (aqua), Lauryl Glucoside, Propylene Glycol, Cocamidopropyl Betaine, PPG-2 Hydroxyethyl Cocamide, Xanthan Gum, Citric Acid, Tetrasodium EDTA, Bis-Diglyceryl Polyacyladipate-2

Principal Display Package Labeling

RECOVERY
ANTISEPTIC
SKIN PREP

VEGAN-FRIENDLY
FREE OF ALCOHOL, PARABENS,
FRAGRANCES & DYES

30 FL. OZ. (900 mL)

NDC: 49436-377-30

recoveryaftercare.com
@recoveryaftercare

Distributed by
Recovery Aftercare, Inc.
Hanover, MD 21076

Made in Canada
©Recovery Aftercare, Inc. 2020

res